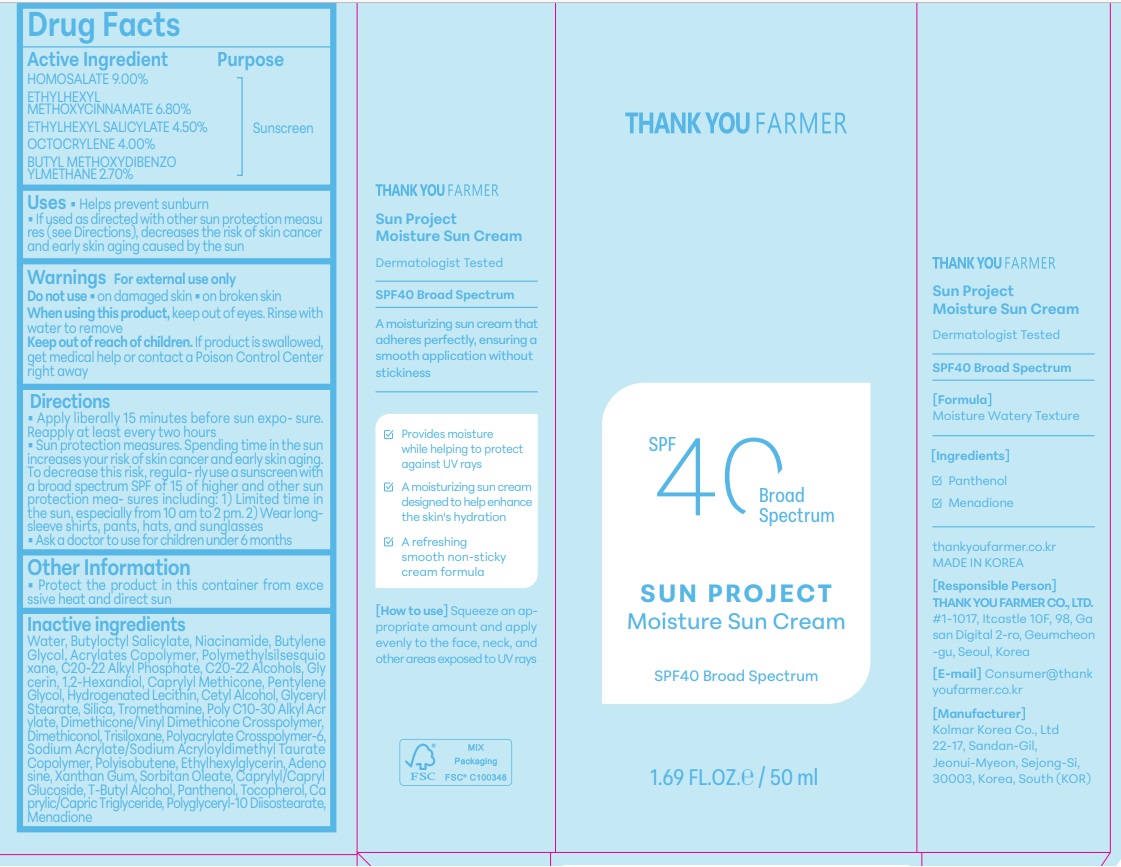 DRUG LABEL: THANKYOU FARMER Sun Project Soothing Sun
NDC: 70618-062 | Form: LOTION
Manufacturer: THANK YOU FARMER CO., LTD
Category: otc | Type: HUMAN OTC DRUG LABEL
Date: 20250311

ACTIVE INGREDIENTS: HOMOSALATE 4.5 g/50 mL; OCTOCRYLENE 2 g/50 mL; OCTISALATE 2.25 g/50 mL; OCTINOXATE 3.4 g/50 mL; AVOBENZONE 1.35 g/50 mL
INACTIVE INGREDIENTS: GLYCERIN; HYDROGENATED SOYBEAN LECITHIN; AMMONIUM ACRYLOYLDIMETHYLTAURATE; BUTYLENE GLYCOL; CAPRYLYL TRISILOXANE; MEDIUM-CHAIN TRIGLYCERIDES; SODIUM ACRYLATE/SODIUM ACRYLOYLDIMETHYLTAURATE COPOLYMER (4000000 MW); XANTHAN GUM; ETHYLHEXYLGLYCERIN; DIMETHICONE/VINYL DIMETHICONE CROSSPOLYMER (SOFT PARTICLE); BEHENYL ACRYLATE POLYMER; PENTYLENE GLYCOL; CAPRYLYL/CAPRYL OLIGOGLUCOSIDE; SORBITAN OLEATE DECYLGLUCOSIDE CROSSPOLYMER; POLYGLYCERYL-10 ISOSTEARATE; PANTHENOL; BUTYLOCTYL SALICYLATE; CETYL ALCOHOL; BUTYL ACRYLATE/METHYL METHACRYLATE/METHACRYLIC ACID COPOLYMER (18000 MW); WATER; C20-22 ALCOHOLS; ADENOSINE; C20-22 ALKYL PHOSPHATE; SILICON DIOXIDE; 1,2-HEXANEDIOL; POLYMETHYLSILSESQUIOXANE (4.5 MICRONS); TOCOPHEROL; TROMETHAMINE; GLYCERYL STEARATE SE; NIACINAMIDE; HYDROGENATED POLYISOBUTENE (1300 MW); MENADIONE; DIMETHICONOL (100000 CST); TRISILOXANE; TERT-BUTYL ALCOHOL

Active Ingredient

Active Ingredient:HOMOSALATE 9%, ETHYLHEXYL METHOXYCINNAMATE 6.8%, ETHYLHEXYL SALICYLATE 4.5%, OCTOCRYLENE 4%, BUTYL METHOXYDIBENZOYLMETHANE 2.7%

Purpose

Purpose-Sunscreen, Uses-Helps prevent sunburn

Uses

Apply Liberally 15 minutes before sun exposure. Reapply at least every two hours Sun Protection measures. Spending time in the sun increases your risk of skin cancer and early skin aging. To Decrease this risk, regularly use a sunscreen with a broad spectrum SP of 15 of higher and other sun protection measures including: 1)Limied time in the sun, especially from 10am to 2pm. 2) Wear Long-sleeve shirts, pants, hats, and sunglasses. Ask a doctor to use for childer under 6 months

WARNINGS

For external use only Do not use on damaged skin & broken skinWhen using this product, keep out of eyes. Rinse with water to remove. Keep out of reach of children. If product is swallowed, get medical help or contact a Poison Control Center right away

Other Information

Other Information-Protect the product in this container from exce ssive heat and direct sun

Inactive Ingredients

WATER, BUTYLOCTYL SALICYLATE, POLYMETHYLSILSESQUIOXANE, NIACINAMIDE, BUTYLENE GLYCOL, ACRYLATES COPOLYMER, C20-22 ALKYL PHOSPHATE, C2 ALCOHOLS, GLYCERIN, 1,2-HEXANEDIOL, CAPRYLYL METHICONE, PENTYLENE GLYCOL,CETYL ALCOHOL, POLY C10-30 ALKYL ACRYLATE, TROMETHAMINE, GLYC STEARATE, SILICA, DIMETHICONE/VINYL DIMETHICONE CROSSPOLYMER, DIMETHICONOL, TRISILOXANE, POLYACRYLATE CROSSPOLYMER-6, SODIUM ACRYLATE/SODIUM ACRYLOYLDIMETHYL TAURATE COPOLYMER,POLYISOBUTENE, ETHYLHEXYLGLYCERIN, ADENOSINE, XANTHAN GUM, CAPRYLYL/CAPRYL GLUCOSIDE, SORBITAN OLEATE, T-BUTYL ALCOHOL, PANTHENOL, TOCOPHEROL, CAPRYLIC/CAPRIC TRIGLYCERIDE, POLYGLYCERYL-10 DIISOSTEARATE, HYDROGENATED LECITHIN ,MENADIONE

Dosage & administration

Dosage & administration -Apply liberally 15 minutes before sun exposure. Reapply at least every two hours

Indications & Usage

Helps prevent sunburn. If used as directed with other sun protection measures (see Directions), decreases the risk of skin cancer and early skin aging caused by the sun.

Keep Out Of Reach of Children- If product is swallowed, get medical help or contact a Poison Control Center right away

PACKAGE LABEL

Package Label Principal Display Panel-Thank you Farmer, SPF40 Broad Spectrum. Sun Project Moisture Sun Cream Sunscreen, SPF40 Broad Spectrum, 1.69 FL.OZ/50ml